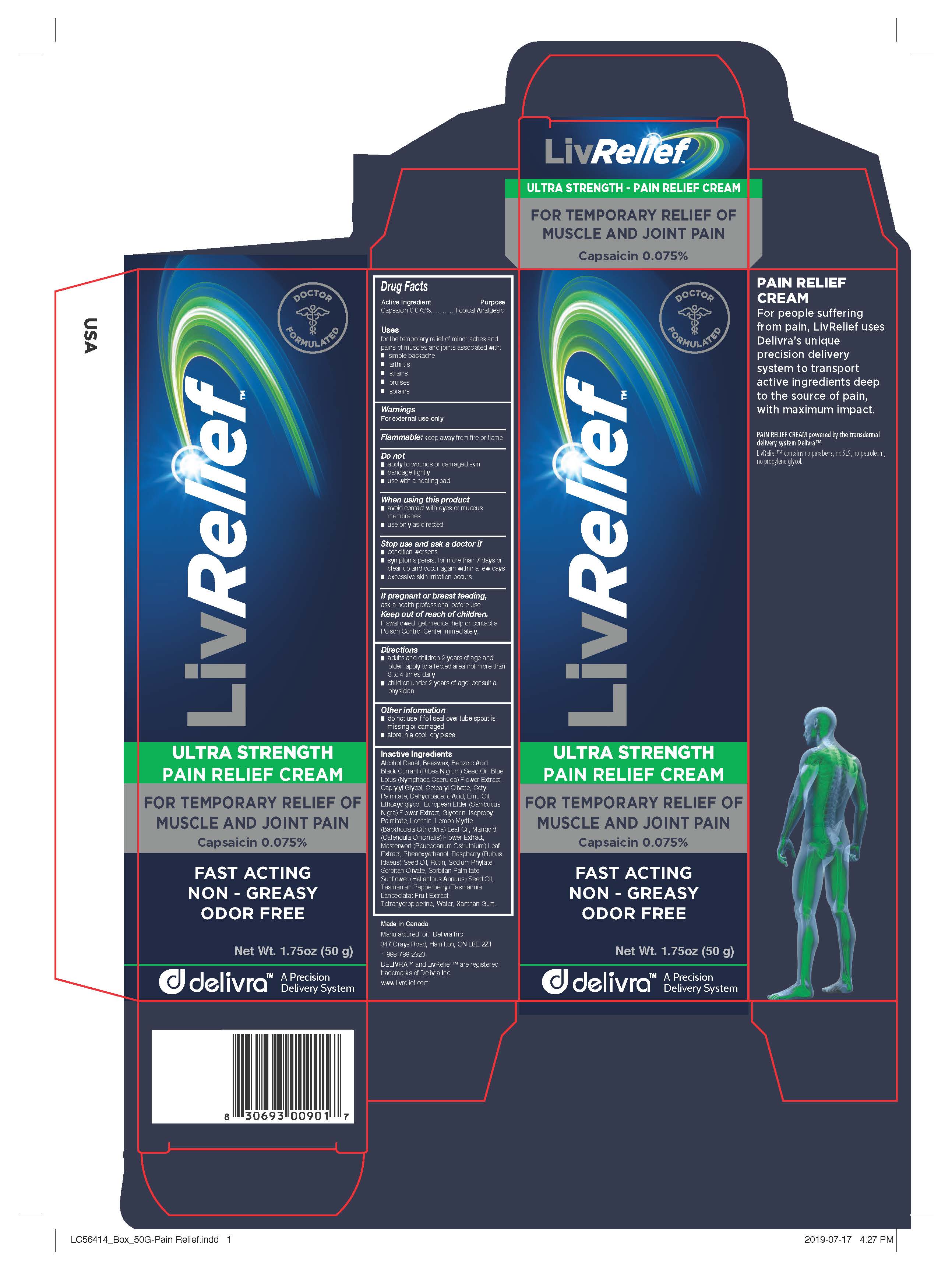 DRUG LABEL: LivRelief
NDC: 42903-008 | Form: CREAM
Manufacturer: LivCorp Inc.
Category: otc | Type: HUMAN OTC DRUG LABEL
Date: 20190728

ACTIVE INGREDIENTS: CAPSAICIN 0.0375 g/50 g
INACTIVE INGREDIENTS: ALCOHOL; BACKHOUSIA CITRIODORA LEAF OIL; YELLOW WAX; BENZOIC ACID; CALENDULA OFFICINALIS FLOWER; CAPRYLYL GLYCOL; CETEARYL OLIVATE; CETYL PALMITATE; DEHYDROACETIC ACID; EMU OIL; RUBUS IDAEUS SEED; GLYCERIN; SUNFLOWER OIL; ISOPROPYL PALMITATE; LECITHIN, SOYBEAN; NYMPHAEA CAERULEA FLOWER; PEUCEDANUM OSTRUTHIUM LEAF; PHENOXYETHANOL; RIBES NIGRUM SEED OIL; RUTIN; SAMBUCUS NIGRA FLOWER; PHYTATE SODIUM; SORBITAN OLIVATE; SORBITAN MONOPALMITATE; TASMANNIA LANCEOLATA FRUIT; TETRAHYDROPIPERINE; WATER; XANTHAN GUM

Drug Facts

Active Ingredient

Capsaicin 0.075%

Purpose

Capsaicin 0.075%..............Topical Analgesic

Uses

for the temporary relief of minor aches and pains of muscles and joints associated with:

- simple backache
- arthritis
- strains
- bruises
- sprains

Warnings

For external use only.

Flammable: keep away from fire or flame.

Do not

- apply to wounds or damaged skin
- bandage tightly
- use with a heating pad

When using this product

- avoid contact with eyes or mucous membranes
- use only as directed

Stop use and ask a doctor if

- condition worsens
- symptoms persist for more than 7 days or clear up and occur again within a few days
- excessive skin irritation occurs

PREGNANCY OR BREAST FEEDING

If pregnant or breast feeding, ask a health professional before use.

Keep out of reach of children. If swallowed, get medical help or contact a Poison Control Center immediately.

Directions

- adults and children 2 years of age and older: apply to affected area not more than 3 to 4 times daily
- children under 2 years of age: consult a physician

Other information

- do not use if foil seal over tube spout is missing or damaged
- store in a cool, dry place

Inactive Ingredients

Alcohol Denat, Beeswax, Benzoic Acid, Black Currant (Ribes Nigrum) Seed Oil, Blue Lotus (Nymphaea Caerulea) Flower Extract,
Caprylyl Glycol, Cetearyl Olivate, Cetyl Palmitate, Dehydroacetic Acid, Emu Oil, Ethoxydiglycol, European Elder (Sambucus
Nigra) Flower Extract, Glycerin, Isopropyl Palmitate, Lecithin, Lemon Myrtle (Backhousia Citriodora) Leaf Oil, Marigold
(Calendula Officinalis) Flower Extract, Masterwort (Peucedanum Ostruthium) Leaf Extract, Phenoxyethanol, Raspberry (Rubus
Idaeus) Seed Oil, Rutin, Sodium Phytate, Sorbitan Olivate, Sorbitan Palmitate, Sunflower (Helianthus Annuus) Seed Oil,
Tasmanian Pepperberry (Tasmannia Lanceolata) Fruit Extract, Tetrahydropiperine, Water, Xanthan Gum.

Manufactured for LivCorp Inc.

Made in Canada
Manufactured for: Delivra Inc
347 Grays Road, Hamilton, ON L8E 2Z1
1-888-788-2320
DELIVRA™ and LivRelief™ are registered
trademarks of Delivra Inc.
www.livrelief.com

Side Panel

PAIN RELIEF CREAM

For people suffering from pain, LivRelief uses Delivra's unique precision delivery system to transport active ingredients deep to the source of pain, with maximum impact.

PAIN RELIEF CREAM powered by the transdermal delivery system Delivra™

LivRelief™ contains no parabens, no SLS, no petroleum, no propylene glycol.

Principal Display Panel

Doctor Formulated

Liv Relief

ULTA STRENGTH

PAIN RELIEF CREAM

FOR TEMPORARY RELIEF OF MUSCLE AND JOINT PAIN

Capsaicin 0.075%

FAST ACTING

NON-GREASY

ODOR FREE

Net Wt. 1.75oz (50 g)

delivra

A Precision Delivery System